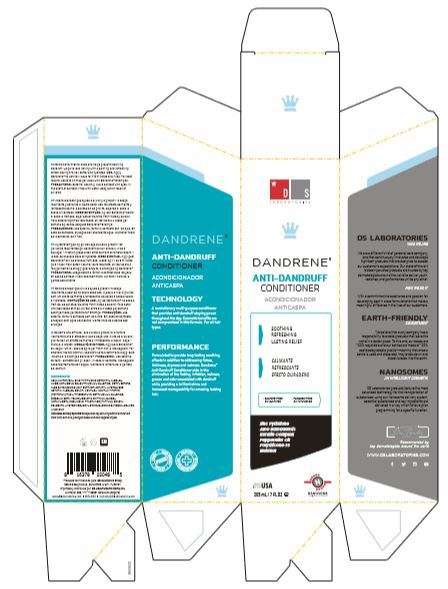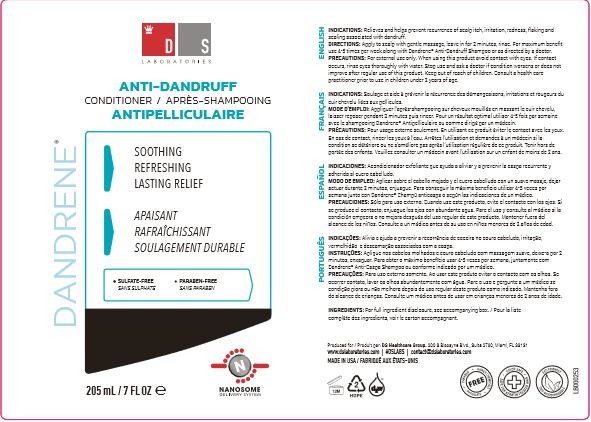 DRUG LABEL: Dandrene
NDC: 72249-001 | Form: LOTION
Manufacturer: Divine Skin Laboratories S.A. de C.V.
Category: otc | Type: HUMAN OTC DRUG LABEL
Date: 20201130

ACTIVE INGREDIENTS: PYRITHIONE ZINC 10 mg/1 g
INACTIVE INGREDIENTS: WATER; CETOSTEARYL ALCOHOL; AMODIMETHICONE (1300 CST); BEHENTRIMONIUM CHLORIDE; CETYL ESTERS WAX; ALOE VERA LEAF; AMINO ACIDS, HAIR KERATIN; ALCOHOL; MENTHOL; PEPPERMINT OIL; TRIDECETH-12; CETRIMONIUM CHLORIDE; EDETATE DISODIUM ANHYDROUS; POLYSILICONE-15; CAPRYLYL GLYCOL; METHYLISOTHIAZOLINONE; BENZYL BENZOATE; HYDROXYISOHEXYL 3-CYCLOHEXENE CARBOXALDEHYDE; LIMONENE, (+)-

Dandrene Conditioner